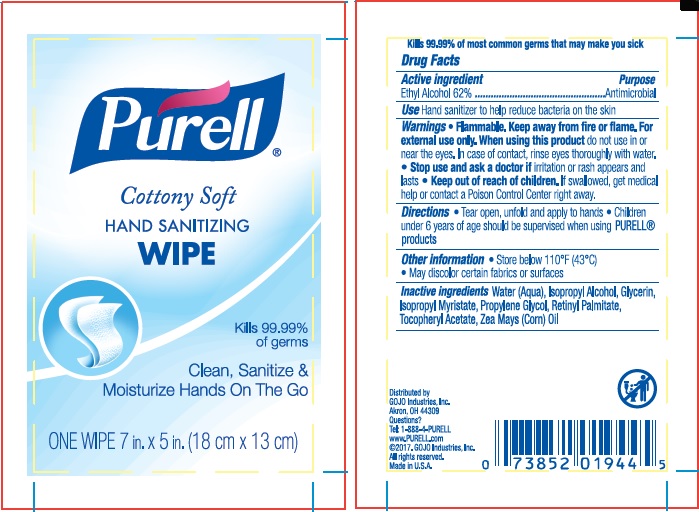 DRUG LABEL: PURELL Cottony Soft Hand Sanitizing Wipe
NDC: 21749-364 | Form: CLOTH
Manufacturer: GOJO Industries, Inc.
Category: otc | Type: HUMAN OTC DRUG LABEL
Date: 20241212

ACTIVE INGREDIENTS: ALCOHOL 62 mL/100 mL
INACTIVE INGREDIENTS: WATER; ISOPROPYL ALCOHOL; GLYCERIN; BEHENTRIMONIUM CHLORIDE; ALOE VERA LEAF; ALKYL (C12-15) BENZOATE; COCAMIDOPROPYL PG-DIMONIUM CHLORIDE PHOSPHATE; ISOPROPYL MYRISTATE; PROPYLENE GLYCOL; VITAMIN A PALMITATE; .ALPHA.-TOCOPHEROL ACETATE, D-; AMINOMETHYLPROPANOL; CORN OIL; METHYLPARABEN

PURELL Cottony Soft Hand Sanitizing Wipe

Active ingredient

Ethyl alcohol 62%

Purpose

Antimicrobial

Use

- Hand sanitizer to help reduce bacteria on the skin

Warnings

Flammable. Keep away from fire or flame.

For external use only

When using this product

do not use in or near the eyes. In case of contact, rinse eyes thoroughly with water.

Stop use and ask a doctor

if irritation or rash appears and lasts

Keep Out of Reach of Children

If swallowed, get medical help or contact a Poison Control Center right away.

Directions

- Tear open, unfold and apply to hands
- Children under 6 years of age should be supervised when using PURELL

Other information

- Store below 110°F (43°C)
- May discolor certain fabrics or surfaces

Questions?

- Call 1-800-321-9647 Monday through Friday 8:30 AM to 5:00 PM
- www.PURELL.com

Inactive ingredients

Water (Aqua), Isopropyl Alcohol, Glycerin, Acetamidopropyl Trimonium Chloride, Aloe Barbadensis Leaf Juice, C12-15 Alkyl Benzoate, Cocamidopropyl PG-Dimonium Chloride Phosphate, Isopropyl Myristate, Propylene Glycol, Retinyl Palmitate, Tocopheryl Acetate, Zea Mays (Corn) Oil, Acrylates/C10-30 Alkyl Acrylate Crosspolymer, Aminomethyl Propanol, Fragrance (Parfum), Methylparaben